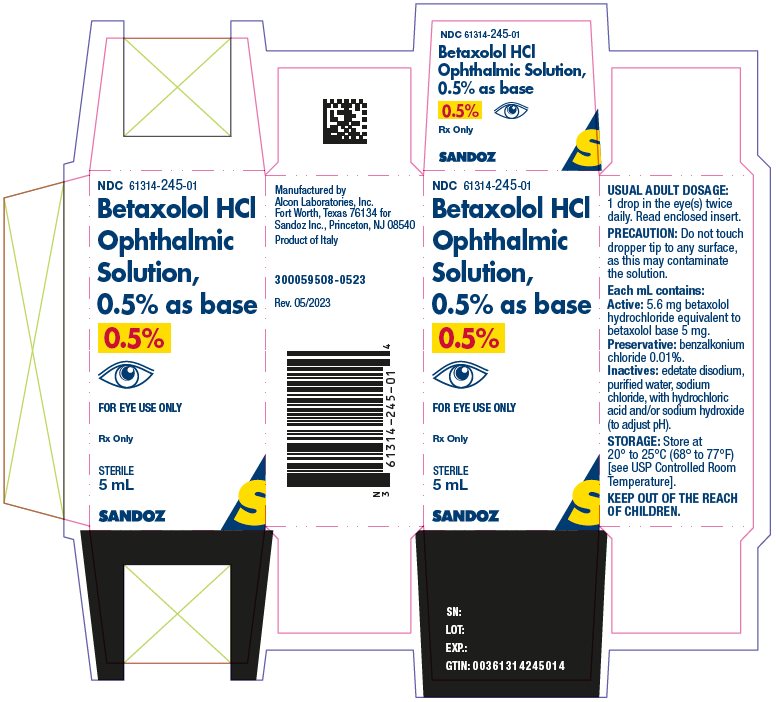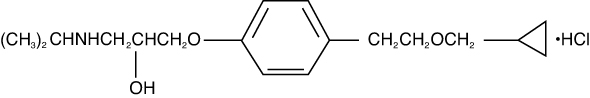 DRUG LABEL: Betaxolol Hydrochloride
NDC: 61314-245 | Form: SOLUTION/ DROPS
Manufacturer: Sandoz Inc
Category: prescription | Type: HUMAN PRESCRIPTION DRUG LABEL
Date: 20231031

ACTIVE INGREDIENTS: BETAXOLOL HYDROCHLORIDE 5.6 mg/1 mL
INACTIVE INGREDIENTS: BENZALKONIUM CHLORIDE; EDETATE DISODIUM; SODIUM CHLORIDE; HYDROCHLORIC ACID; SODIUM HYDROXIDE; WATER

Betaxolol Hydrochloride Ophthalmic Solution, 0.5% as base
Sterile
Rx Only

DESCRIPTION

Betaxolol Hydrochloride Ophthalmic Solution contains betaxolol hydrochloride, a cardioselective beta-adrenergic receptor blocking agent, in a sterile isotonic solution. Betaxolol hydrochloride is a white, crystalline powder, soluble in water, with a molecular weight of 343.89. The chemical structure is presented below:

Empirical Formula:

C18H29NO3•HCl

Chemical Name:

(±)-1-[p-[2-(Cyclopropylmethoxy)ethyl]phenoxy]-3-(isopropylamino)-2-propanol hydrochloride.

Each mL contains: Active: 5.6 mg betaxolol hydrochloride equivalent to betaxolol base 5 mg. Preservative: benzalkonium chloride 0.01%. Inactives: edetate disodium, purified water, sodium chloride, with hydrochloric acid and/or sodium hydroxide (to adjust pH).

CLINICAL PHARMACOLOGY

Betaxolol Hydrochloride, a cardioselective (beta-1-adrenergic) receptor blocking agent, does not have significant membrane-stabilizing (local anesthetic) activity and is devoid of intrinsic sympathomimetic action. Orally administered beta-adrenergic blocking agents reduce cardiac output in healthy subjects and patients with heart disease. In patients with severe impairment of myocardial function, beta-adrenergic receptor antagonists may inhibit the sympathetic stimulatory effect necessary to maintain adequate cardiac function.

When instilled in the eye, Betaxolol Hydrochloride Ophthalmic Solution has the action of reducing elevated as well as normal intraocular pressure, whether or not accompanied by glaucoma. Ophthalmic betaxolol has minimal effect on pulmonary and cardiovascular parameters.

Ophthalmic betaxolol (one drop in each eye) was compared to timolol and placebo in a three-way crossover study challenging nine patients with reactive airway disease who were selected on the basis of having at least a 15% reduction in the forced expiratory volume in one second (FEV1) after administration of ophthalmic timolol. Betaxolol HCl had no significant effect on pulmonary function as measured by FEV1, Forced Vital Capacity (FVC) and FEV1/VC. Additionally, the action of isoproterenol, a beta stimulant, administered at the end of the study was not inhibited by ophthalmic betaxolol. In contrast, ophthalmic timolol significantly decreased these pulmonary functions.

FEV1 - Percent Change from Baseline^1

 | Means
 | Betaxolol 1.0%a | Timolol 0.5% | Placebo
Baseline | 1.6 | 1.4 | 1.4
60 Minutes | 2.3 | -25.7* | 5.8
120 Minutes | 1.6 | -27.4* | 7.5
240 Minutes | -6.4 | -26.9* | 6.9
Isoproterenolb | 36.1 | -12.4* | 42.8

^1Schoene, R. B. et al., Am. J. Ophthal. 97:86, 1984.

aTwice the clinical concentration.

bInhaled at 240 minutes; measurement at 270 minutes.

*Timolol statistically different from betaxolol and placebo (p < 0.05).

No evidence of cardiovascular beta-adrenergic blockade during exercise was observed with betaxolol in a double-masked, three-way crossover study in 24 normal subjects comparing ophthalmic betaxolol, timolol and placebo for effect on blood pressure and heart rate. Mean arterial blood pressure was not affected by any treatment; however, ophthalmic timolol produced a significant decrease in the mean heart rate.

Mean Heart Rates^1

 | TREATMENT
Bruce Stress Exercise Test
Minutes | Betaxolol 1%a | Timolol 0.5% | Placebo
0 | 79.2 | 79.3 | 81.2
2 | 130.2 | 126.0 | 130.4
4 | 133.4 | 128.0* | 134.3
6 | 136.4 | 129.2* | 137.9
8 | 139.8 | 131.8* | 139.4
10 | 140.8 | 131.8* | 141.3

^1Atkins, J. M. et al., Am. J. Oph. 99:173-175, Feb., 1985.

aTwice the clinical concentration.

*Mean pulse rate significantly lower for timolol than betaxolol or placebo (p < 0.05).

Clinical Studies

Optic nerve head damage and visual field loss are the result of a sustained elevated intraocular pressure and poor ocular perfusion. Betaxolol Hydrochloride Ophthalmic Solution has the action of reducing elevated as well as normal intraocular pressure, and the mechanism of ocular hypotensive action appears to be a reduction of aqueous production as demonstrated by tonography and aqueous fluorophotometry. The onset of action with Betaxolol Hydrochloride Ophthalmic Solution can generally be noted within 30 minutes and the maximal effect can usually be detected 2 hours after topical administration. A single dose provides a 12-hour reduction in intraocular pressure. Clinical observation of glaucoma patients treated with Betaxolol Hydrochloride Ophthalmic Solution for up to three years shows that the intraocular pressure lowering effect is well maintained.

Clinical studies show that topical Betaxolol Hydrochloride Ophthalmic Solution reduces mean intraocular pressure 25% from baseline. In trials using 22 mmHg as a generally accepted index of intraocular pressure control, Betaxolol Hydrochloride Ophthalmic Solution was effective in more than 94% of the population studied, of which 73% were treated with the beta blocker alone. In controlled, double-masked studies, the magnitude and duration of the ocular hypotensive effect of Betaxolol Hydrochloride Ophthalmic Solution and ophthalmic timolol solution were clinically equivalent.

Betaxolol Hydrochloride Ophthalmic Solution has also been used successfully in glaucoma patients who have undergone a laser trabeculoplasty and have needed additional long-term ocular hypotensive therapy.

Betaxolol Hydrochloride Ophthalmic Solution has been well tolerated in glaucoma patients wearing hard or soft contact lenses and in aphakic patients.

Betaxolol Hydrochloride Ophthalmic Solution does not produce miosis or accommodative spasm which are frequently seen with miotic agents. The blurred vision and night blindness often associated with standard miotic therapy are not associated with Betaxolol Hydrochloride Ophthalmic Solution. Thus, patients with central lenticular opacities avoid the visual impairment caused by a constricted pupil.

INDICATIONS AND USAGE

Betaxolol Hydrochloride Ophthalmic Solution has been shown to be effective in lowering intraocular pressure and is indicated in the treatment of ocular hypertension and chronic open-angle glaucoma. It may be used alone or in combination with other anti-glaucoma drugs.

In clinical studies, Betaxolol Hydrochloride Ophthalmic Solution was safely used to lower intraocular pressure in 47 patients with both glaucoma and reactive airway disease who were followed for a mean period of 15 months. However, caution should be used in treating patients with severe reactive airway disease or a history of asthma.

CONTRAINDICATIONS

Hypersensitivity to any component of this product. Betaxolol Hydrochloride Ophthalmic Solution is contraindicated in patients with sinus bradycardia, greater than a first degree atrioventricular block, cardiogenic shock, or patients with overt cardiac failure.

WARNING

Topically applied beta-adrenergic blocking agents may be absorbed systemically. The same adverse reactions found with systemic administration of beta-adrenergic blocking agents may occur with topical administration. For example, severe respiratory reactions and cardiac reactions, including death due to bronchospasm in patients with asthma, and rarely death in association with cardiac failure, have been reported with topical application of beta-adrenergic blocking agents.

Betaxolol Hydrochloride Ophthalmic Solution has been shown to have a minor effect on heart rate and blood pressure in clinical studies. Caution should be used in treating patients with a history of cardiac failure or heart block. Treatment with Betaxolol Hydrochloride Ophthalmic Solution should be discontinued at the first signs of cardiac failure.

PRECAUTIONS

Information for Patients

Do not touch dropper tip to any surface as this may contaminate the solution.

Diabetes Mellitus

Beta-adrenergic blocking agents should be administered with caution in patients subject to spontaneous hypoglycemia or to diabetic patients (especially those with labile diabetes) who are receiving insulin or oral hypoglycemic agents. Beta-adrenergic receptor blocking agents may mask the signs and symptoms of acute hypoglycemia.

Thyrotoxicosis

Beta-adrenergic blocking agents may mask certain clinical signs (e.g., tachycardia) of hyperthyroidism. Patients suspected of developing thyrotoxicosis should be managed carefully to avoid abrupt withdrawal of beta-adrenergic blocking agents, which might precipitate a thyroid storm.

Muscle Weakness

Beta-adrenergic blockade has been reported to potentiate muscle weakness consistent with certain myasthenic symptoms (e.g., diplopia, ptosis, and generalized weakness).

Major Surgery

Consideration should be given to the gradual withdrawal of beta-adrenergic blocking agents prior to general anesthesia because of the reduced ability of the heart to respond to beta-adrenergically mediated sympathetic reflex stimuli.

Pulmonary

Caution should be exercised in the treatment of glaucoma patients with excessive restriction of pulmonary function. There have been reports of asthmatic attacks and pulmonary distress during betaxolol treatment. Although rechallenges of some such patients with ophthalmic betaxolol has not adversely affected pulmonary function test results, the possibility of adverse pulmonary effects in patients sensitive to beta-blockers cannot be ruled out.

Risk from Anaphylactic Reaction

While taking beta-blockers, patients with a history of atopy or a history of severe anaphylactic reaction to a variety of allergens may be more reactive to repeated accidental, diagnostic, or therapeutic challenge with such allergens. Such patients may be unresponsive to the usual doses of epinephrine used to treat anaphylactic reactions.

Drug Interactions

Patients who are receiving a beta-adrenergic blocking agent orally and Betaxolol Hydrochloride Ophthalmic Solution should be observed for a potential additive effect either on the intraocular pressure or on the known systemic effects of beta blockade.

Close observation of the patient is recommended when a beta blocker is administered to patients receiving catecholamine-depleting drugs such as reserpine, because of possible additive effects and the production of hypotension and/or bradycardia.

Betaxolol is an adrenergic blocking agent; therefore, caution should be exercised in patients using concomitant adrenergic psychotropic drugs.

Ocular

In patients with angle-closure glaucoma, the immediate treatment objective is to reopen the angle by constriction of the pupil with a miotic agent. Betaxolol has little or no effect on the pupil. When Betaxolol Hydrochloride Ophthalmic Solution is used to reduce elevated intraocular pressure in angle-closure glaucoma, it should be used with a miotic and not alone.

Carcinogenesis, Mutagenesis, Impairment of Fertility

Lifetime studies with betaxolol HCl have been completed in mice at oral doses of 6, 20 or 60 mg/kg/day and in rats at 3, 12 or 48 mg/kg/day; betaxolol HCl demonstrated no carcinogenic effect. Higher dose levels were not tested.

In a variety of in vitro and in vivo bacterial and mammalian cell assays, betaxolol HCl was nonmutagenic.

Pregnancy

Reproduction, teratology, and peri- and postnatal studies have been conducted with orally administered betaxolol HCl in rats and rabbits. There was evidence of drug related postimplantation loss in rabbits and rats at dose levels above 12 mg/kg and 128 mg/kg, respectively. Betaxolol HCl was not shown to be teratogenic, however, and there were no other adverse effects on reproduction at subtoxic dose levels. There are no adequate and well-controlled studies in pregnant women. Betaxolol Hydrochloride Ophthalmic Solution should be used during pregnancy only if the potential benefit justifies the potential risk to the fetus.

Nursing Mothers

It is not known whether betaxolol HCl is excreted in human milk. Because many drugs are excreted in human milk, caution should be exercised when Betaxolol Hydrochloride Ophthalmic Solution is administered to nursing women.

Pediatric Use

Safety and effectiveness in pediatric patients have not been established.

Geriatric Use

No overall differences in safety or effectiveness have been observed between elderly and younger patients.

ADVERSE REACTIONS

The following adverse reactions have been reported in clinical trials with Betaxolol Hydrochloride Ophthalmic Solution.

Ocular

Discomfort of short duration was experienced by one in four patients, but none discontinued therapy; occasional tearing has been reported. Rare instances of decreased corneal sensitivity, erythema, itching sensation, corneal punctate staining, keratitis, anisocoria, edema, and photophobia have been reported.

Additional medical events reported with other formulations of betaxolol include blurred vision, foreign body sensation, dryness of the eyes, inflammation, discharge, ocular pain, decreased visual acuity, and crusty lashes.

Systemic

Systemic reactions following administration of Betaxolol Hydrochloride Ophthalmic Solution 0.5% or Betaxolol Hydrochloride Ophthalmic Suspension 0.25% have been rarely reported. These include:

Cardiovascular

Bradycardia, heart block and congestive failure.

Pulmonary

Pulmonary distress characterized by dyspnea, bronchospasm, thickened bronchial secretions, asthma and respiratory failure.

Central Nervous System

Insomnia, dizziness, vertigo, headaches, depression, lethargy, and increase in signs and symptoms of myasthenia gravis.

Other

Hives, toxic epidermal necrolysis, hair loss and glossitis.

To report SUSPECTED ADVERSE REACTIONS, contact Sandoz Inc., at 1-800-525-8747 or FDA at 1-800-FDA-1088 or www.fda.gov/medwatch.

OVERDOSAGE

No information is available on overdosage of humans. The oral LD50 of the drug ranged from 350-920 mg/kg in mice and 860-1050 mg/kg in rats. The symptoms which might be expected with an overdose of a systemically administered beta-1-adrenergic receptor blocker agent are bradycardia, hypotension and acute cardiac failure. A topical overdose of Betaxolol Hydrochloride Ophthalmic Solution may be flushed from the eye(s) with warm tap water.

DOSAGE AND ADMINISTRATION

The recommended dose is one to two drops of Betaxolol Hydrochloride Ophthalmic Solution in the affected eye(s) twice daily. In some patients, the intraocular pressure lowering responses to Betaxolol Hydrochloride Ophthalmic Solution may require a few weeks to stabilize. As with any new medication, careful monitoring of patients is advised.

If the intraocular pressure of the patient is not adequately controlled on this regimen, concomitant therapy with pilocarpine and other miotics, and/or epinephrine and/or carbonic anhydrase inhibitors can be instituted.

HOW SUPPLIED

Betaxolol Hydrochloride Ophthalmic Solution is a sterile, isotonic, aqueous solution of betaxolol hydrochloride. Supplied as follows: 5, 10 and 15 mL in plastic ophthalmic dispensers.

5 mL: NDC 61314-245-01 15 mL: NDC 61314-245-02

10 mL: NDC 61314-245-03

STORAGE: Store at 20° to 25°C (68° to 77°F) [see USP Controlled Room Temperature].

Rev. May 2023

300059509-0523

Manufactured by

Alcon Laboratories, Inc.

Fort Worth, Texas 76134 for

Sandoz Inc.

Princeton, NJ 08540

PRINCIPAL DISPLAY PANEL

NDC 61314-245-01

Betaxolol HCl

Ophthalmic

Solution,

0.5% as base

0.5%

FOR EYE USE ONLY

Rx Only

STERILE

5 mL

SANDOZ